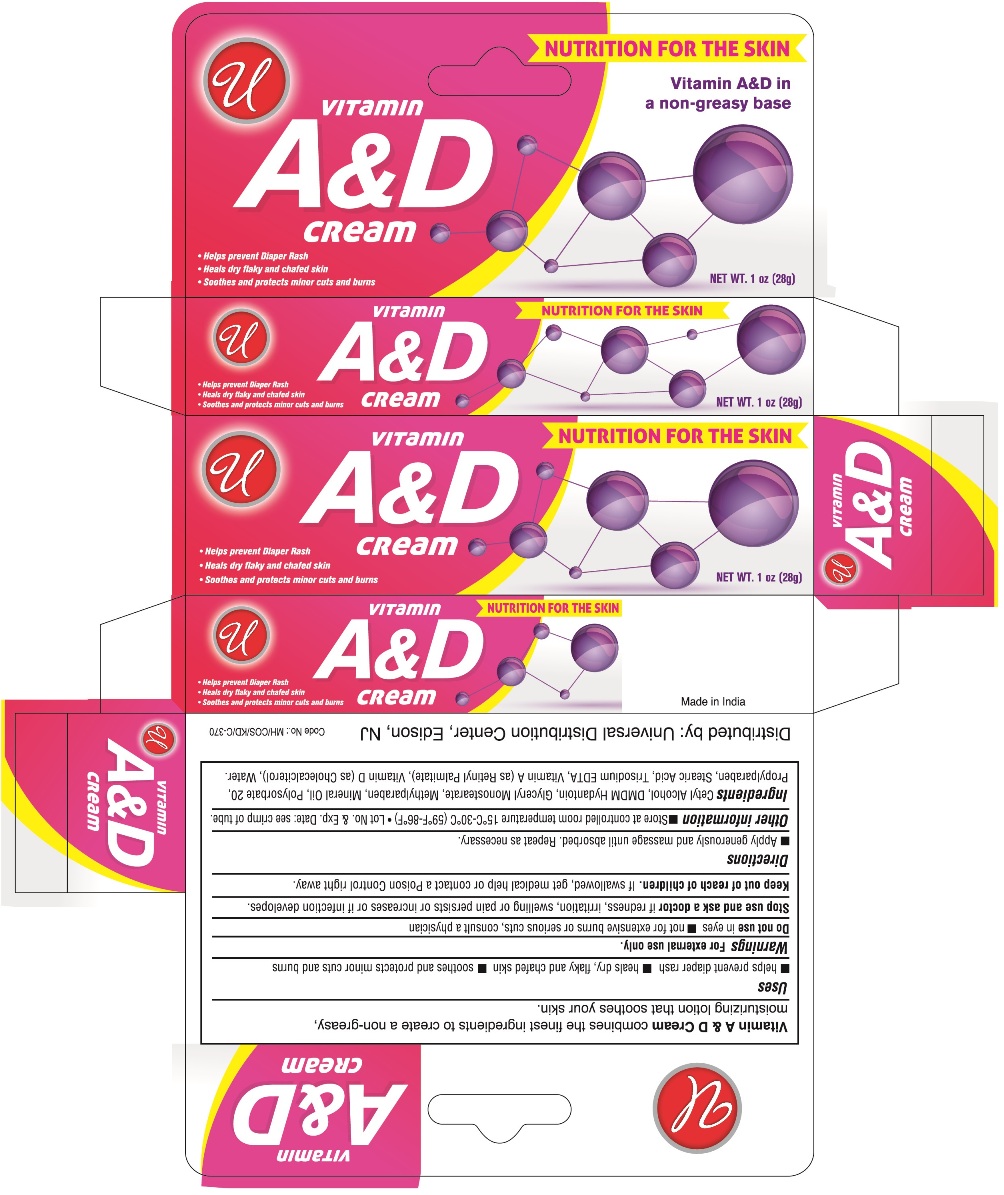 DRUG LABEL: Vitamin A and D
NDC: 52000-026 | Form: CREAM
Manufacturer: Universal Distribution Center LLC
Category: otc | Type: HUMAN OTC DRUG LABEL
Date: 20241017

ACTIVE INGREDIENTS: VITAMIN A 181.8 [iU]/1 g; VITAMIN D 1200 [iU]/1 g
INACTIVE INGREDIENTS: CETYL ALCOHOL; DMDM HYDANTOIN; GLYCERYL MONOSTEARATE; METHYLPARABEN; MINERAL OIL; POLYSORBATE 20; PROPYLPARABEN; STEARIC ACID; EDETATE TRISODIUM; WATER

Vitamin A&D Cream

Active Ingredients

Vitamin A 181.8 IU

Vitamin D 1200 IU

Purpose

Skin protectant

Uses

- helps prevent diaper rash
- heals dry, flaky and chafed skin
- soothes and protects minor cuts and burns

Warnings

For external use only

Do not use in eyes

- not for extensive burns or serious cuts, consult a physician

Stop use and ask a doctor if redness, irritation, swelling or pain persists or increases or if infection develops.

Keep out of reach of children.

If swallowed, get medical help or contact a Poison Control Center right away.

Directions

- Apply generously and massage until absorbed. Repeat as necessary.

Other information

- Store at controlled room temperature 15ºC to 30ºC (59ºF to 86ºF). Lot No. & Exp.Date see crimp of tube.

Inactive ingredients

Cetyl Alcohol, DMDM Hydantoin, Glyceryl Monostearate, Methylparaben, Mineral Oil, Polysorbate 20, Propylparaben, Stearic Acid, Trisodium EDTA, and Water.

PACKAGE LABEL

PRINCIPAL DISPLAY PANEL

Vitamin A&D Cream

NET WT 1 OZ (28 g)